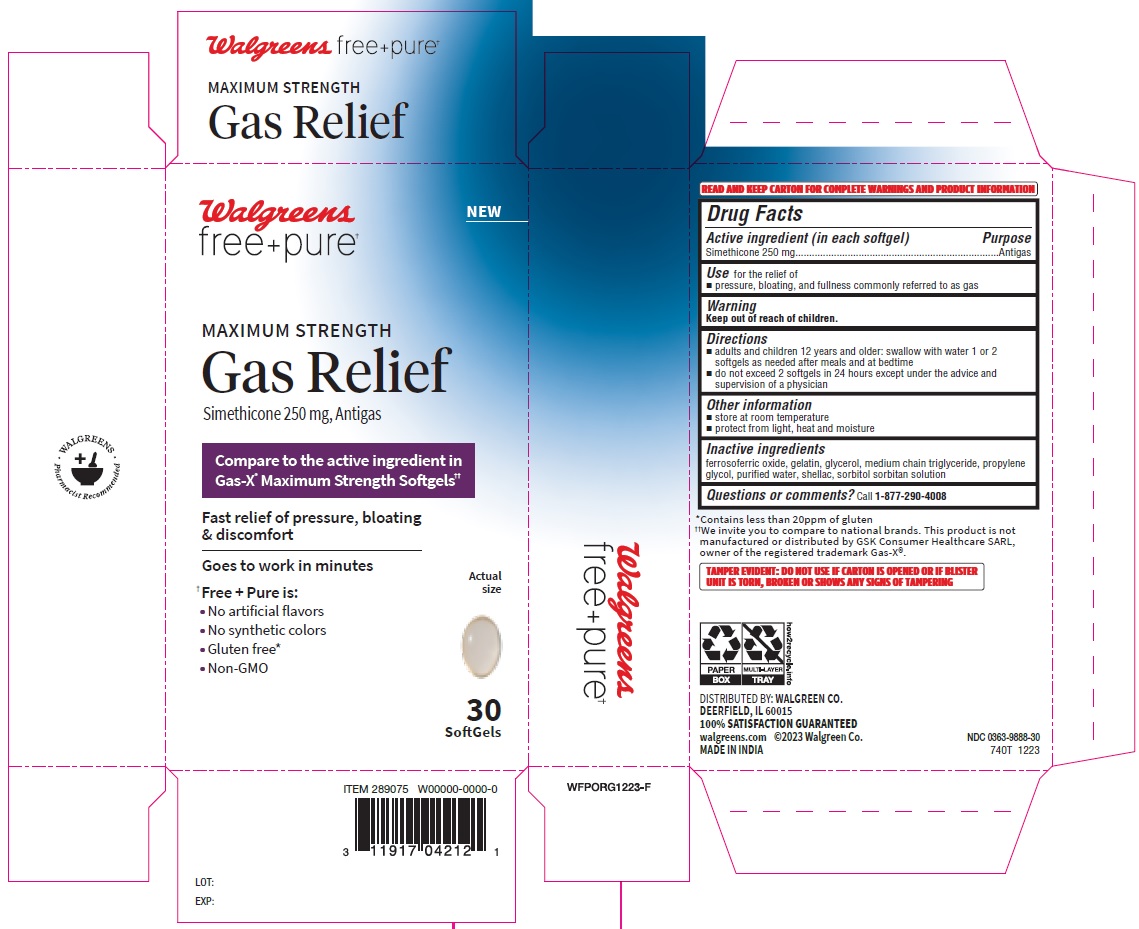 DRUG LABEL: Maximum Strength Gas Relief
NDC: 0363-9888 | Form: CAPSULE, LIQUID FILLED
Manufacturer: WALGREENS
Category: otc | Type: HUMAN OTC DRUG LABEL
Date: 20240306

ACTIVE INGREDIENTS: DIMETHICONE 250 mg/1 1
INACTIVE INGREDIENTS: FERROSOFERRIC OXIDE; PROPYLENE GLYCOL; WATER; SORBITOL; MEDIUM-CHAIN TRIGLYCERIDES; SHELLAC; GELATIN; GLYCERIN; SORBITAN

Walgreens Simethicone 250 mg Capsules Dye Free

Active ingredient (in each softgel)

Simethicone 250 mg

Purpose

Antigas

INDICATIONS AND USAGE

Usefor the relief of

- pressure, bloating, and fullness commonly referred to as gas

Warning

Keep out of reach of children.

Directions

- adults and children 12 years and older: swallow with water 1 or 2 softgels as needed after meals and at bedtime
- do not exceed 2 softgels in 24 hours except under the advice and supervision of a physician

Other information

- store at room temperature
- protect from light, heat and moisture

Inactive ingredients

ferrosoferric oxide, gelatin, glycerol, medium chain triglyceride, propylene glycol, purified water, shellac, sorbitol sorbitan solution

Questions or comments?Call 1-877-290-4008